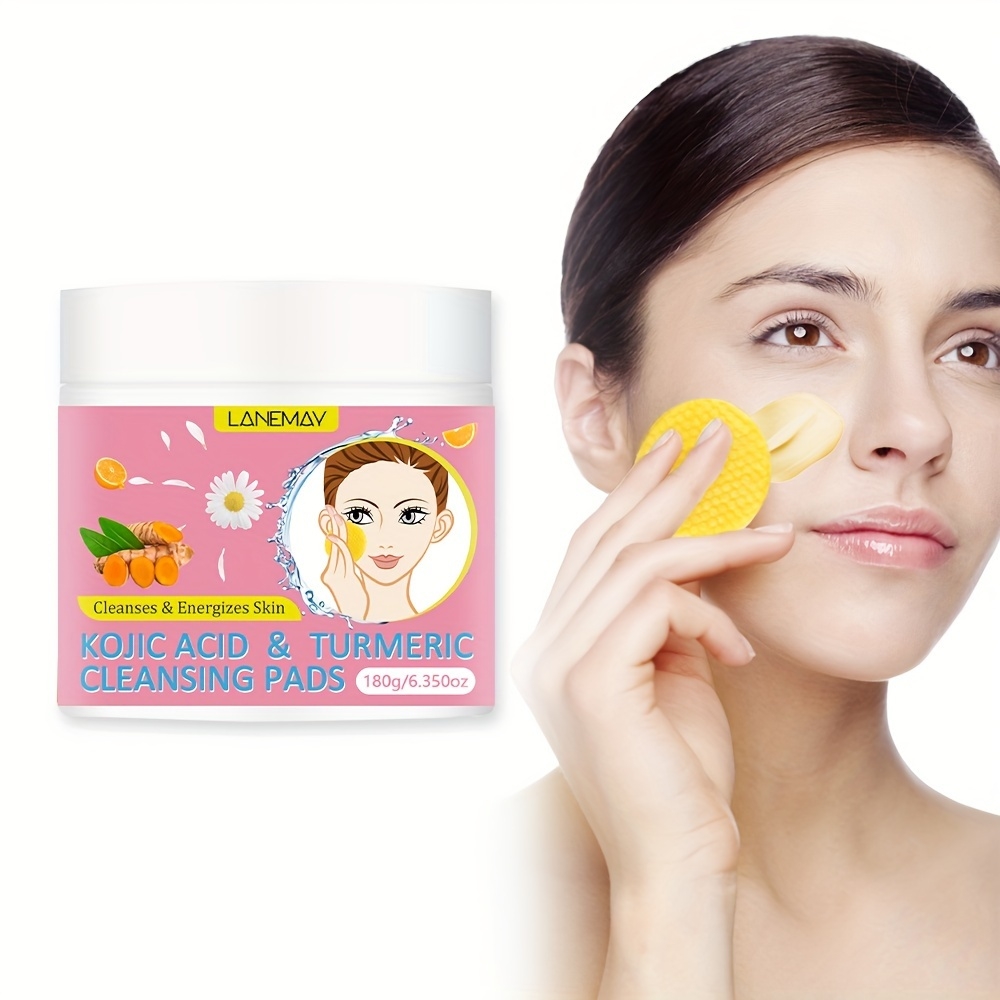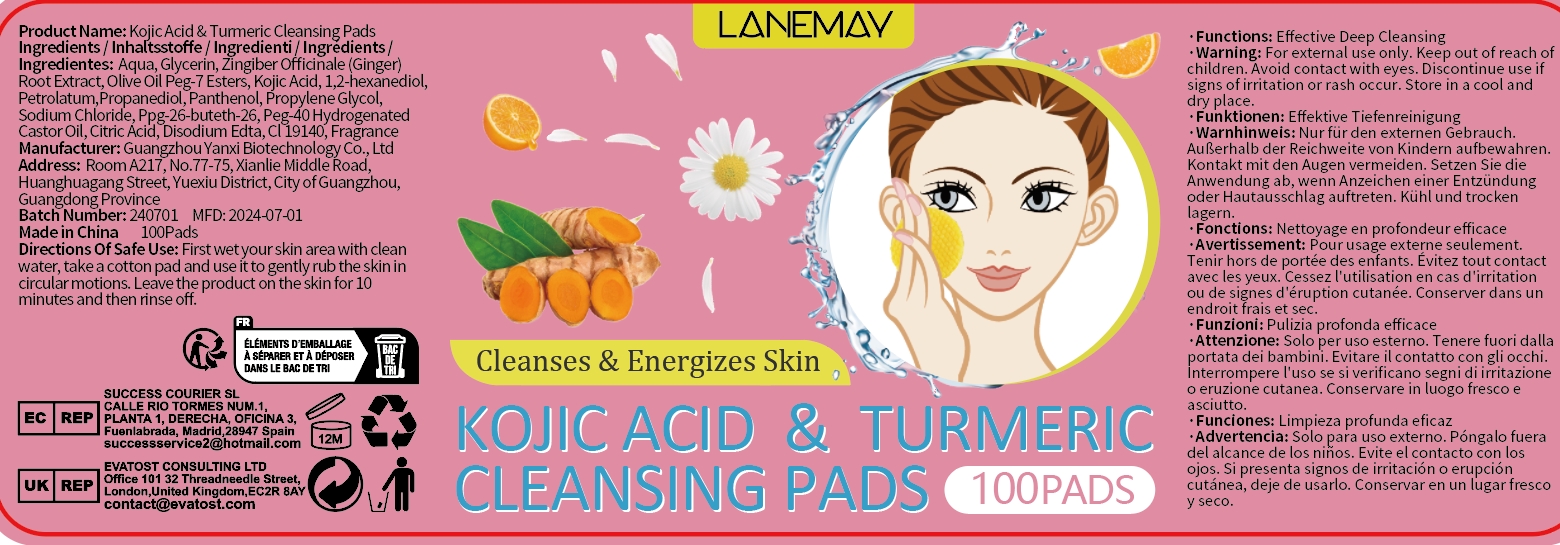 DRUG LABEL: Kojic Acid Turmeric Cleansing Pads
NDC: 84025-278 | Form: FILM
Manufacturer: Guangzhou Yanxi Biotechnology Co., Ltd
Category: otc | Type: HUMAN OTC DRUG LABEL
Date: 20241203

ACTIVE INGREDIENTS: PETROLATUM 6 mg/180 g; GLYCERIN 8 mg/180 g
INACTIVE INGREDIENTS: WATER

WARNINGS

Keep out of children

INACTIVE INGREDIENT

Aqua

INDICATIONS AND USAGE

For daily skin care

Keep out of childen

PURPOSE

Cleanings face skin